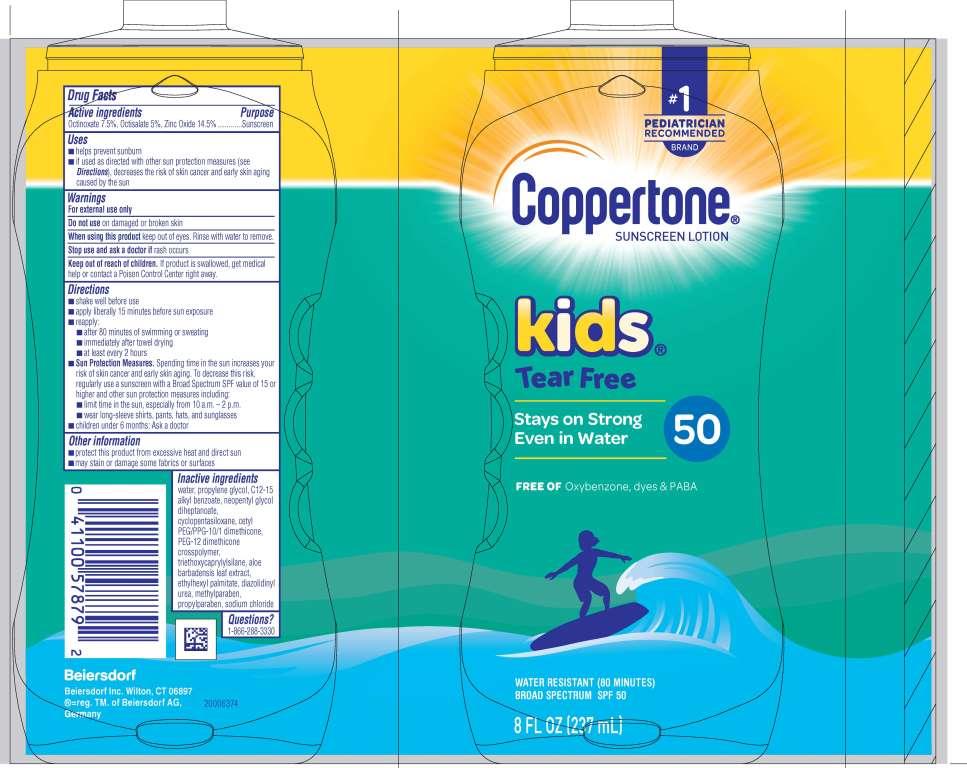 DRUG LABEL: Coppertone Kids Tear Free Mineral Sunscreen SPF 50
NDC: 66800-2450 | Form: LOTION
Manufacturer: Beiersdorf Inc
Category: otc | Type: HUMAN OTC DRUG LABEL
Date: 20251231

ACTIVE INGREDIENTS: ZINC OXIDE 14.5 g/100 g; OCTISALATE 5 g/100 g; OCTINOXATE 7.5 g/100 g
INACTIVE INGREDIENTS: PEG-12 DIMETHICONE/PPG-20 CROSSPOLYMER; ALOE VERA LEAF; ETHYLHEXYL PALMITATE; PROPYLPARABEN; SODIUM CHLORIDE; NEOPENTYL GLYCOL DIHEPTANOATE; TRIETHOXYCAPRYLYLSILANE; METHYLPARABEN; DIAZOLIDINYL UREA; WATER; CYCLOMETHICONE 5; PROPYLENE GLYCOL; ALKYL (C12-15) BENZOATE; CETYL PEG/PPG-10/1 DIMETHICONE (HLB 1.5)

Kids Tear Free Mineral Lotion SPF 50

Active ingredients

Octinoxate 7.5%, Octisalate 5%, Zinc Oxide 14.5%

Purpose

Sunscreen

Uses

■ helps prevent sunburn

■ if used as directed with other sun protection measures (see Directions), decreases the risk of skin cancer and early skin aging caused by the sun

Warnings

For external use only

Do not useon damaged or broken skin

WHEN USING

When using this productkeep out of eyes. Rinse with water to remove.

Stop use and ask a doctor ifrash occurs

Keep out of reach of children.If product is swallowed, get medical help or contact a Poison Control Center right away.

Directions

■ shake well before use

■ apply liberally 15 minutes before sun exposure

■ reapply:

■ after 80 minutes of swimming or sweating

■ immediately after towel drying

■ at least every 2 hours

■ Sun Protection Measures.Spending time in the sun increases your risk of skin cancer and early skin aging. To decrease this risk, regularly use a sunscreen with a Broad Spectrum SPF value of 15 or higher and other sun protection measures including:

■ limit time in the sun, especially from 10 a.m. – 2 p.m.

■ wear long-sleeve shirts, pants, hats, and sunglasses

■ children under 6 months: Ask a doctor

Other information

■ protect this product from excessive heat and direct sun

■ may stain or damage some fabrics or surfaces

Inactive ingredients

water, propylene glycol, C12-15 alkyl benzoate, neopentyl glycol diheptanoate, cyclopentasiloxane, cetyl PEG/PPG-10/1 dimethicone, PEG-12 dimethicone crosspolymer, triethoxycaprylylsilane, aloe barbadensis leaf extract, ethylhexyl palmitate, diazolidinyl urea, methylparaben, propylparaben, sodium chloride

Questions

1-866-288-3330

PACKAGE LABEL

#1 Pediatrician Recommended Brand

Coppertone®Sunscreen Lotion

kids Tear Free

Stays on Strong Even in Water 50

Free Of oxybenzone, dyes & PABA

Water Resistant (80 Minutes)

Broad Spectrum SPF 50

8 FL OZ (237 mL)